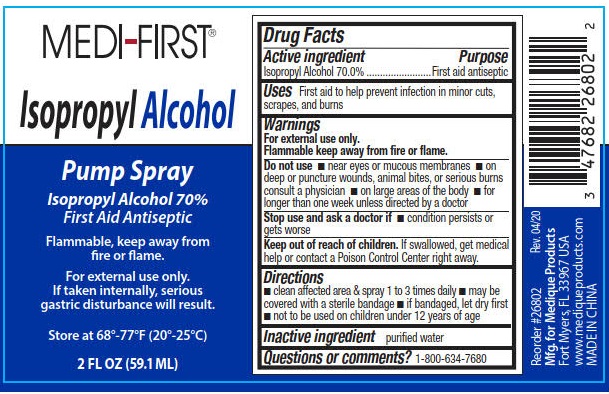 DRUG LABEL: Medi-First Isopropyl Alcohol
NDC: 47682-262 | Form: SPRAY
Manufacturer: Unifirst First Aid Corporation
Category: otc | Type: HUMAN OTC DRUG LABEL
Date: 20250908

ACTIVE INGREDIENTS: ISOPROPYL ALCOHOL 70 mL/100 mL
INACTIVE INGREDIENTS: WATER

Medi-First 70% IPA - Nantong

Drug Facts

Active ingredient

Isopropyl Alcohol 70.0%

Purpose

First aid antiseptic

Uses

First aid to help prevent infection in minor cuts, scrapes, and burns

Warnings

For external use only.

Flammable keep away from fire or flame.

Do not use

- near eyes or mucous membranes
- on deep or puncture wounds, animal bites, or serious burns consult a physician
- on large areas of the body
- for longer than one week unless directed by a doctor

Stop use and ask a doctor if

- condition persists or gets worse

Keep out of reach of children.

If swallowed, get medical help or contact a Poison Control Center right away.

Directions

- clean affected area and spray 1 to 3 times daily
- may be covered with a sterile bandage
- if bandaged, let dry first
- not to be used on children under 12 years of age

Inactive ingredient

purified water

Questions or comments?

1-800-634-7680

PACKAGE LABEL

Medi-First®

Isppropyl Alcohol

Pump Spray

Isopropyl Alcohol 70%

First Aid Antiseptic

Flammable, keep away from fire or flame.

For external use only.

If taken internally, serious gastric disturbance will result.

Store at 68º-77ºF (20º-25ºC)

2 FL OZ (59.1 ML)